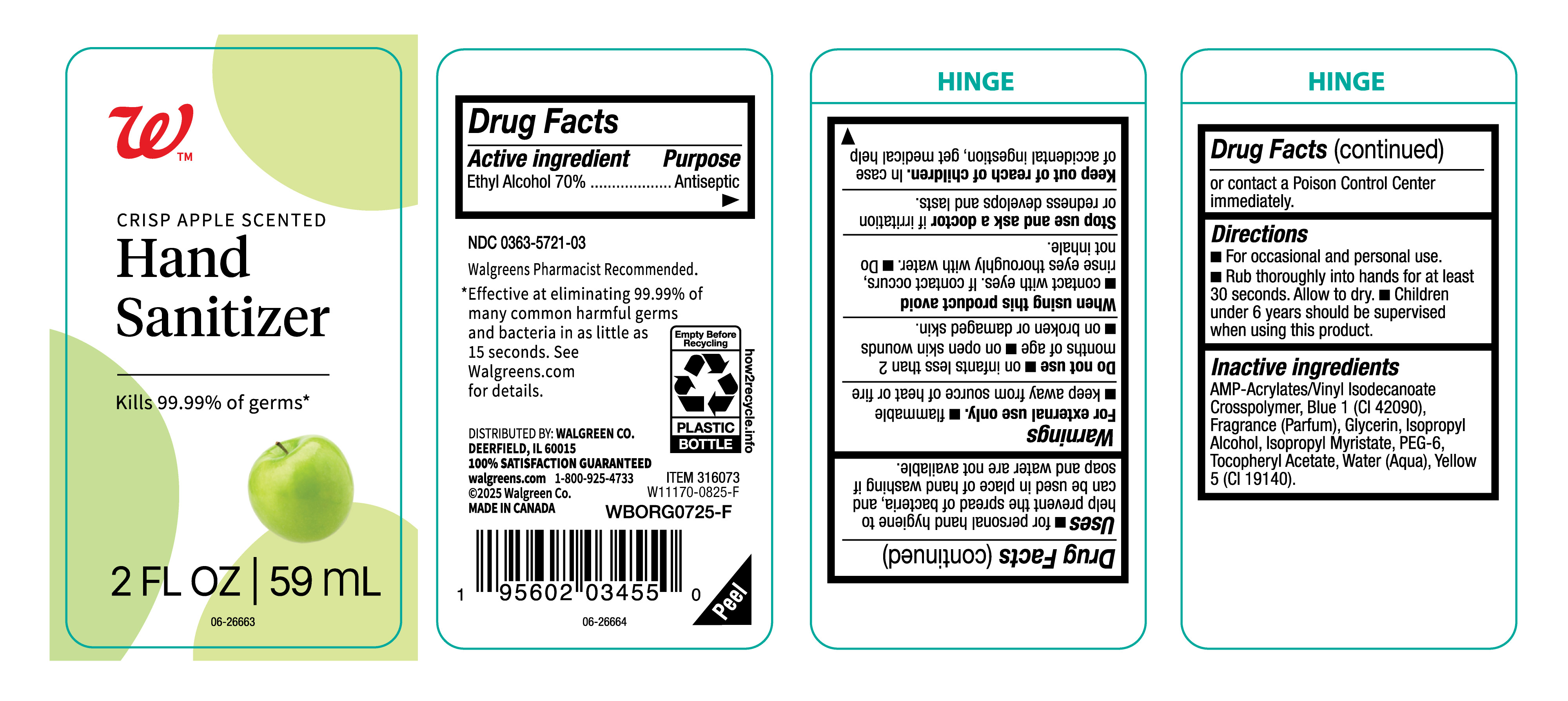 DRUG LABEL: Walgreens
NDC: 0363-5721 | Form: GEL
Manufacturer: Walgreen
Category: otc | Type: HUMAN OTC DRUG LABEL
Date: 20250903

ACTIVE INGREDIENTS: ALCOHOL 700 mg/1 mL
INACTIVE INGREDIENTS: FRAGRANCE CLEAN ORC0600327; ACRYLATES/VINYL ISODECANOATE CROSSPOLYMER (10000 MPA.S NEUTRALIZED AT 0.5%); WATER; PEG-6; ISOPROPYL ALCOHOL; GLYCERIN; ISOPROPYL MYRISTATE; .ALPHA.-TOCOPHEROL ACETATE; YELLOW 5; BLUE 1

Walgreens 0363-5721-03

Active Ingredient

Ethyl Alcohol (70%)

Purpose

Antiseptic

Uses

- For Personal hand hygiene to help prevent the spread of bacteria, and can be used in place of hand washing if soap and water are not available.

Warnings

For External use only.

- Flammable
- Keep away from source of heat or fire.

Do not use

- On infants less than 2 months of age.
- On open skin wounds.
- On broken or damaged skin.

When using this product avoid

- Contact with eyes. If contact occurs, rinse eyes thoroughly with water.
- Do not inhale.

Stop use and ask a doctor

if irritation or redness develops and lasts.

Keep out of reach of children

In case of accidental ingestion, get medical help or contact a Poison Control Center immediately.

Directions

- For occassional andpersonal use.
- Rub throughly into hands for at least 30 seconds. Allow to dry.
- Children under 6 years should be supervised when using this product.

Inactive Ingredients

AMP Acrylates/Vinyl Isodecanoate Crosspolymer, Blue 1 (CI 42090), Fragrance (Parfum), Glycerin, Isopropyl Alcohol, Isopropyl Myristate, PEG-6, Tocopheryl Acetate, Water (Aqua), Yellow 5 (CI 19140),